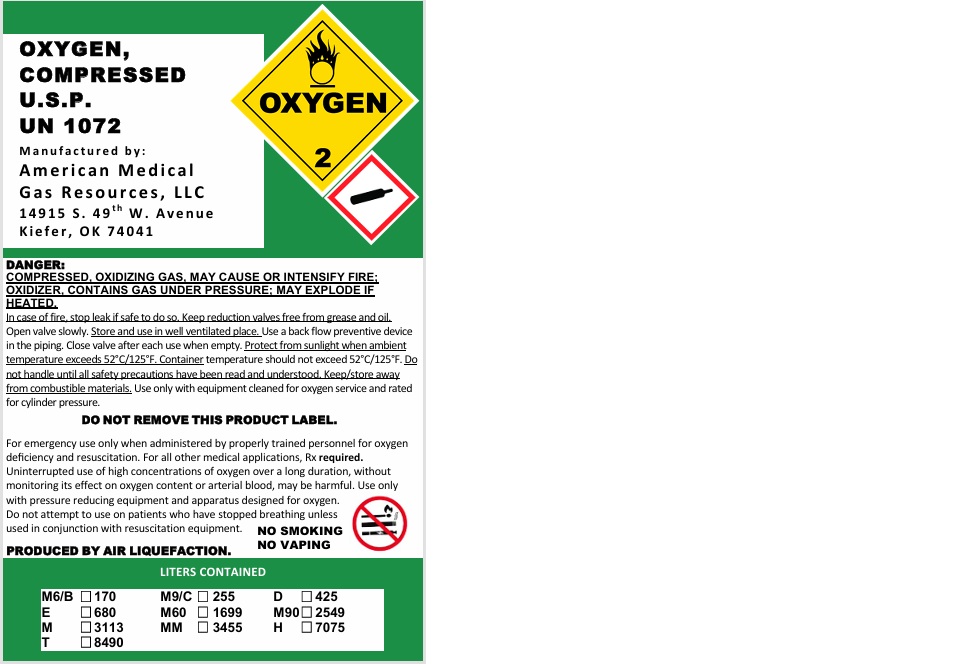 DRUG LABEL: Oxygen
NDC: 81313-001 | Form: GAS
Manufacturer: AMERICAN MEDICAL GAS RESOURCES LLC
Category: prescription | Type: HUMAN PRESCRIPTION DRUG LABEL
Date: 20251208

ACTIVE INGREDIENTS: OXYGEN 992 mL/1 L

Oxygen

PACKAGE LABEL

OXYGEN, COMPRESSED U.S.P.

UN 1072

Manufactured by:

American Medical Gas Resources, LLC

14915 S. 49th W. Avenue

Kiefer, OK 74041

DANGER: COMPRESSED, OXIDIZING GAS, MAY CAUSER OR INTENSIFY FIRE; OXIDIZER. CONTAINS GAS UNDER PRESSURE; MAY EXPLODE IF HEATED.

In case of fire, stop leak if safe to do so. Keep reduction valves free from grease and oil. Open valve slowly. Store and use in well ventilated place. Use a back flow preventive device in the piping. Close valve after each use when empty. Protect from sunlight when ambient temperature exceeds 52 C / 125 F. Container temperature should not exceed 52 C / 125 F. Do not handle until all safety precautions have been read and understood. Keep/store away from combustible materials. Use only with equipment cleaned for oxygen service and rated for cylinder pressure.

DO NOT REMOVE THIS PRODUCT LABEL.

For emergency use only when administered by properly trained personnel for oxygen deficiency and resuscitation. For all other medical applications, Rx required. Uninterrupted use of high concentrations of oxygen over a long duration, without monitoring its effect on oxygen content or arterial blood, may be harmful. Use only with pressure reducing equipment and apparatus designed for oxygen. Do not attempt to use on patients who have stopped breathing unless used in conjunction with resuscitation equipment.

PRODUCED BY AIR LIQUEFACTION.

NO SMOKING

NO VAPING

LITERS CONTAINED

M6/B 170 M9/C 255 D 425

E 680 M60 1699 M90 2549

M 3113 MM 3455 H 7075

T 8490